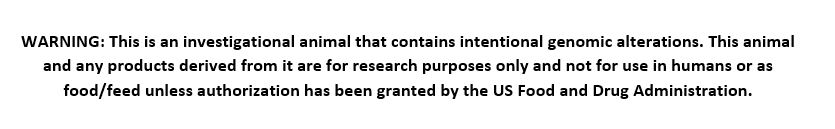 DRUG LABEL: Oncopig Cancer Model
NDC: 86150-0001 | Form: NOT APPLICABLE
Manufacturer: Sus Clinicals, Inc
Category: other | Type: INTENTIONAL ANIMAL GENOMIC ALTERATION LABEL
Date: 20251013

ACTIVE INGREDIENTS: Cre-inducible Neo-KRASG12D-TP53R167H rDNA construct in the ITPRID1 gene in cross-bred swine 1 [arb'U]/1 [arb'U]

Oncopig Cancer Model

Cre-inducible Neo-KRASG12D-TP53R167H rDNA construct in the ITPRID1 gene in cross-bred swine

This is an investigational animal that contains intentional genomic alterations. This animal and any products derived from it are for research purposes only and not for use in humans or as food/feed unless authorization has been granted by the US Food and Drug Administration.